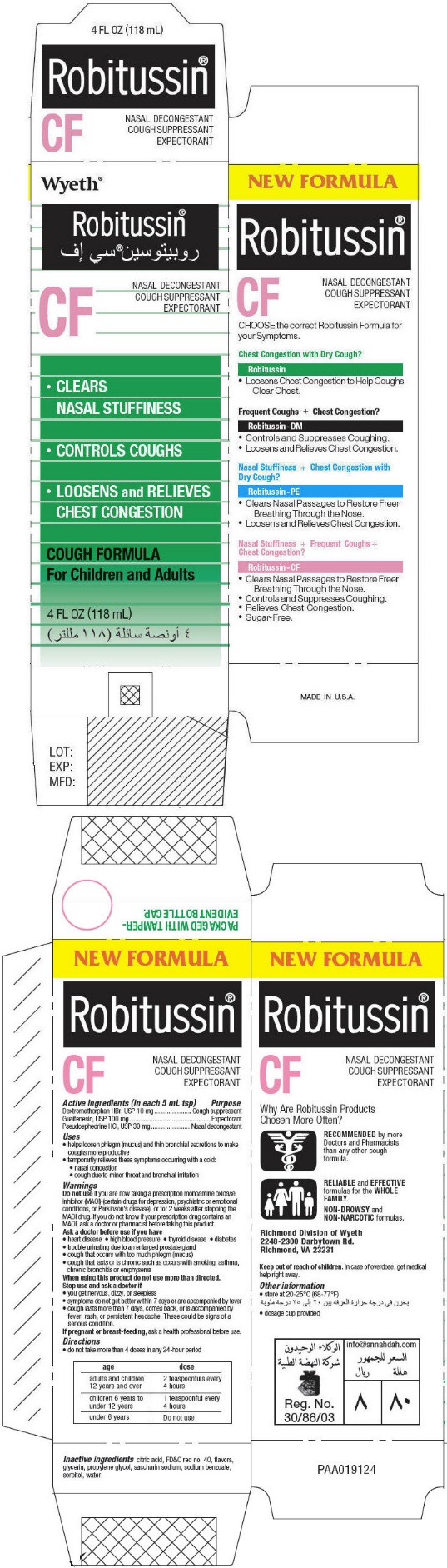 DRUG LABEL: Robitussin CF
NDC: 0031-8678 | Form: LIQUID
Manufacturer: Haleon US Holdings LLC
Category: otc | Type: HUMAN OTC DRUG LABEL
Date: 20240424

ACTIVE INGREDIENTS: DEXTROMETHORPHAN HYDROBROMIDE 10 mg/5 mL; GUAIFENESIN 100 mg/5 mL; PSEUDOEPHEDRINE HYDROCHLORIDE 30 mg/5 mL
INACTIVE INGREDIENTS: CITRIC ACID MONOHYDRATE; FD&C RED NO. 40; GLYCERIN; PROPYLENE GLYCOL; SACCHARIN SODIUM; SODIUM BENZOATE; SORBITOL; WATER

Robitussin®CF

ACTIVE INGREDIENT

Active ingredients (in each 5 mL tsp) | Purpose
Dextromethorphan HBr, USP 10 mg | Cough suppressant
Guaifenesin, USP 100 mg | Expectorant
Pseudoephedrine HCl, USP 30 mg | Nasal decongestant

Uses

- helps loosen phlegm (mucus) and thin bronchial secretions to make coughs more productive
- temporarily relieves these symptoms occurring with a cold:
  - nasal congestion
  - cough due to minor throat and bronchial irritation

Warnings

DO NOT USE

Do not useif you are now taking a prescription monoamine oxidase inhibitor (MAOl) (certain drugs for depression, psychiatric or emotional conditions, or Parkinson's disease), or for 2 weeks after stopping the MAOl drug. If you do not know if your prescription drug contains an MAOl, ask a doctor or pharmacist before taking this product.

Ask a doctor before use if you have

- heart disease
- high blood pressure
- thyroid disease
- diabetes
- trouble urinating due to an enlarged prostate gland
- cough that occurs with too much phlegm (mucus)
- cough that lasts or is chronic such as occurs with smoking, asthma, chronic bronchitis or emphysema

When using this product do not use more than directed.

Stop use and ask a doctor if

- you get nervous, dizzy, or sleepless
- symptoms do not get better within 7 days or are accompanied by fever
- cough lasts more than 7 days, comes back, or is accompanied by fever, rash, or persistent headache. These could be signs of a serious condition.

PREGNANCY OR BREAST FEEDING

If pregnant or breast-feeding,ask a health professional before use.

Directions

- do not take more than 4 doses in any 24-hour period

age | dose
adults and children 12 years and over | 2 teaspoonfuls every 4 hours
children 6 years to under 12 years | 1 teaspoonful every 4 hours
under 6 years | Do not use

Inactive ingredients

citric acid, FD&C red no. 40, flavors, glycerin, propylene glycol, saccharin sodium, sodium benzoate, sorbitol, water.

Keep out of reach of children.In case of overdose, get medical help right away.

Other information

- store at 20-25°C (68-77°F)
- dosage cup provided

QUESTIONS

MADE IN U.S.A.

PRINCIPAL DISPLAY PANEL - 118 mL Bottle Carton

Wyeth®

Robitussin®

CF

NASAL DECONGESTANT
COUGH SUPPRESSANT
EXPECTORANT

- CLEARS
  NASAL STUFFINESS
- CONTROLS COUGHS
- LOOSENS and RELIEVES
  CHEST CONGESTION

COUGH FORMULA
For Children and Adults

4 FL OZ (118 mL)